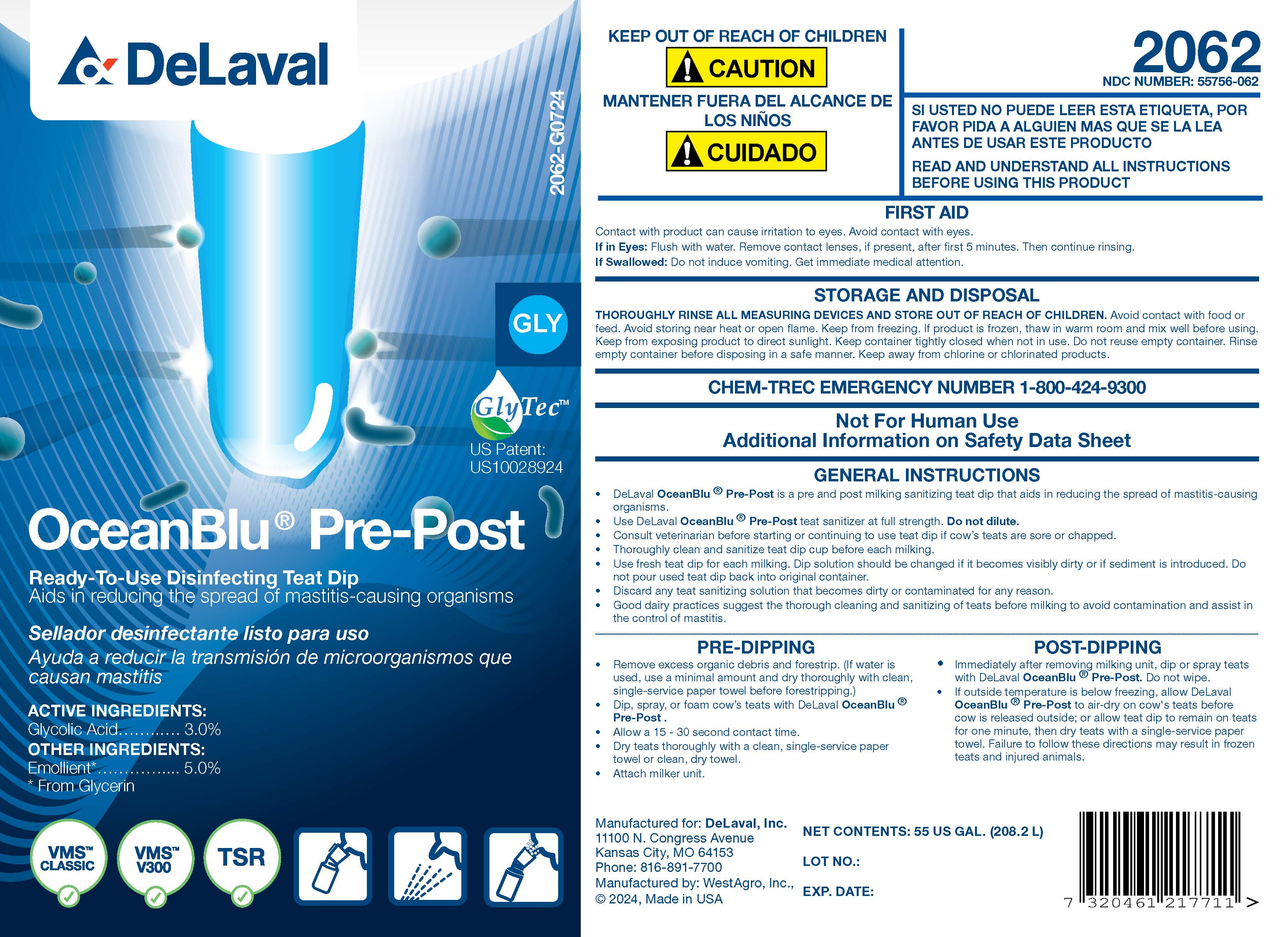 DRUG LABEL: OceanBlu Pre-Post
NDC: 55756-062 | Form: SOLUTION
Manufacturer: DeLaval
Category: animal | Type: OTC ANIMAL DRUG LABEL
Date: 20240924

ACTIVE INGREDIENTS: GLYCOLIC ACID 30.4 g/1 L
INACTIVE INGREDIENTS: GLYCERIN; XANTHAN GUM; C9-11 PARETH-8; FD&C BLUE NO. 1; SODIUM HYDROXIDE; WATER; 1-OCTANESULFONIC ACID; SODIUM C14-16 OLEFIN SULFONATE

DeLaval
OceanBlu® Pre-Post

PURPOSE

Ready-To-Use Disinfecting Teat Dip

Aids in reducing the spread of mastitis-causing organisms

ACTIVE INGREDIENTS:

Glycolic Acid .................... 3.0%

INACTIVE INGREDIENT

OTHER INGREDIENTS:

Emollient* ...................... 5.0%

* From Glycerin

GlyTecTM

US Patent: US10028924

KEEP OUT OF REACH OF CHILDREN

!CAUTION

MANTENER FUERA DEL ALCANCE DE LOST NINOS

!CUIDADO

SI USTED NO PUEDE LEER ESTA ETIQUETA, POR FAVOR PIDA A ALGUIEN MAS QUE SE LA LEA ANTES DE USAR ESTE PRODUCTO

READ AND UNDERSTAND ALL INSTRUCTIONS BEFORE USING THIS PRODUCT

FIRST AID

Contact with eyes can cause irritation to eyes. Avoid contact with eyes.

If in Eyes: Flush with water. Remove contact lenses, if present, after first 5 minutes. Then continue rinsing.

If Swallowed: Do not induce vomiting. Get immediate medical attention.

STORAGE AND DISPOSAL

THOROUGHLY RINSE ALL MEASURING DEVICES AND STORE OUT OF REACH OF CHILDREN. Avoid contact with food or feed. Avoid storing near heat or open flame. Keep from freezing. If product is frozen, thaw in warm room and mix well before using. Keep from exposing product to direct sunlight. Keep container tightly closed when not in use. Do not reuse empty container. Rinse empty container before disposing in a safe manner. Keep away from chlorine or chlorinated products.

CHEM-TREC EMERGENCY NUMBER 1-800-424-9300

Not for Human Use

Additional Information on Safety Data Sheet

GENERAL INSTRUCTIONS

- DeLaval OceanBlu® Pre-Post is a pre and post milking sanitizing teat dip that aids in reducing the spread of mastitis-causing organisms.
- Use DeLaval Ocean Blu® Pre-Post teat sanitizer at full strength. Do not dilute.
- Consult veterinarian before starting or continuing to use teat dip if cow's teats are sore or chapped.
- Thoroughly clean and sanitize teat dip cup before each milking.
- Use fresh teat dip for each milking. Dip solution should be changed if it becomes visibly dirty or if sediment is introduced. Do not pour used teat dip back into original container.
- Discard any teat sanitizing solution that becomes dirty or contaminated for any reason.
- Good dairy practices suggest the thorough cleaning and sanitizing of teats before milking to avoid contamination and assist in the control of mastitis.

PRE-DIPPING

- Remove excess organic debris and forestrip. (if water is used, use a minimal amount and dry thoroughly with clean, single-service paper towel before forestripping.)
- Dip, spray, or foam cow's teats with DeLaval OceanBlu® Pre-Post.
- Allow a 15 - 30 second contact time.
- Dry teats thoroughly with a clean, single-service paper towel or clean, dry towel.
- Attach milker unit.

POST-DIPPING

- Immediately after removing milking unit, dip or spray teats with DeLaval OceanBlu® Pre-Post. Do not wipe.
- If outside temperature is below freezing, allow DeLaval OceanBlu® Pre-Post to air-dry on cow's teats before cow is released outside; or allow teat dip to remain on teats for one minute, then dry teats with a single-service paper towel. Failure to follow these directions may result in frozen teats and injured animals.

Manufactured for: DeLaval, Inc.
11100 N. Congress Avenue
Kansas City, MO 64153
Phone: 816-891-7700
Manufactured by: WestAgro, Inc.
©2024, Made in USA

NET CONTENTS:

LOT NO.:

EXP. DATE:

PACKAGE LABEL

Add image transcription here...